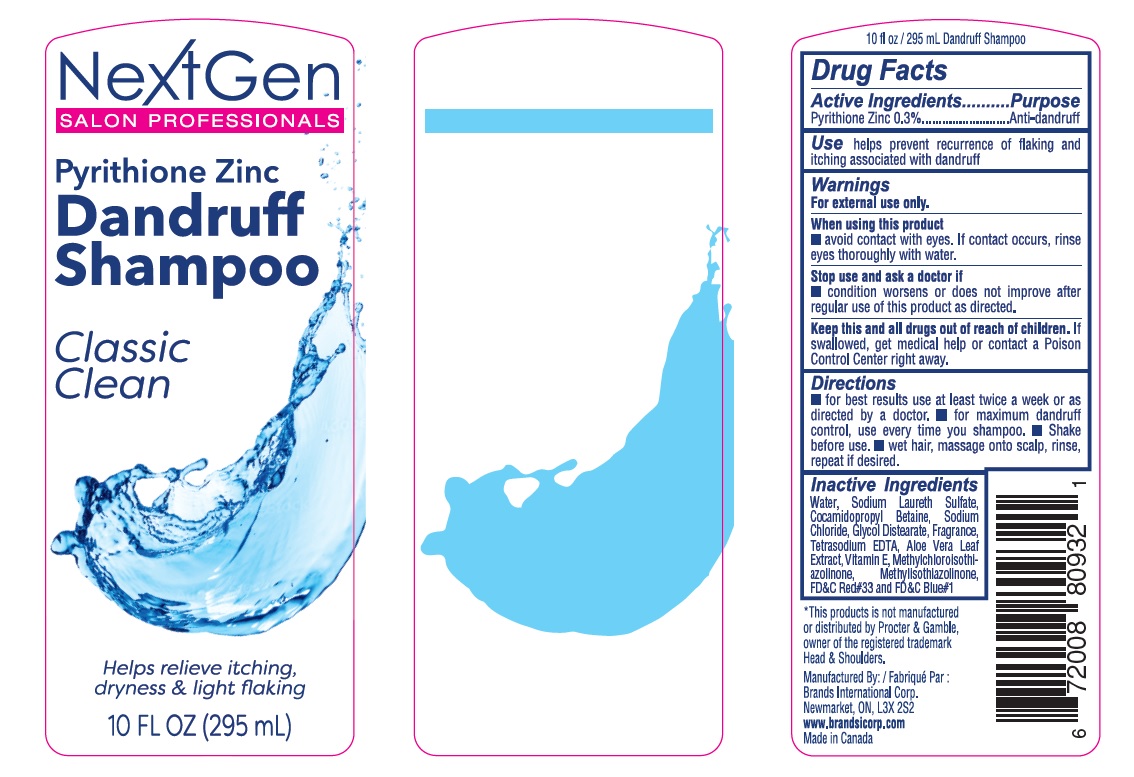 DRUG LABEL: PYRITHIONE ZINC
NDC: 50157-125 | Form: SHAMPOO
Manufacturer: BRANDS INTERNATIONAL
Category: otc | Type: HUMAN OTC DRUG LABEL
Date: 20230804

ACTIVE INGREDIENTS: PYRITHIONE ZINC 0.3 g/100 mL
INACTIVE INGREDIENTS: WATER; SODIUM CHLORIDE; GLYCOL DISTEARATE; EDETATE SODIUM; ALOE VERA LEAF; D&C RED NO. 33; BASIC BLUE 1; .ALPHA.-TOCOPHEROL; COCAMIDOPROPYL BETAINE; METHYLISOTHIAZOLINONE; SODIUM LAURYL SULFATE; METHYLCHLOROISOTHIAZOLINONE

Next Gen Dandruff Shampoo

DOSAGE AND ADMINISTRATION

For maximum dandruff control, use every time you shampoo.
Wet hair, massage unto scalp, rinse, and repeat if desired.

For best results use at least twice a week or as directed by a doctor.

WARNINGS

For external use only.

INACTIVE INGREDIENT

Water, Sodium Laureth Sulfate, Cocamidopropyl Betaine, Sodium Chloride, Glycol Distearate, Aloe vera Leaf Extract, Parfum, Vitamin E, Methylchloroisothiazolinone,Methylisothiazolinone, FD&C Blue#1 ,FD&C Red#33.

INDICATIONS AND USAGE

Helps prevent recurrence of flaking and itching associated with dandruff.

Keep Out of children’s reach.

PURPOSE

Anti-dandruff

ACTIVE INGREDIENT

Pyrithione Zinc 0.3%

STOP USE

Condition worsens or does not improve after regular use of this product as directed

WHEN USING

Avoid contact with eyes. If contact occurs, rinse eyes thoroughly with water.